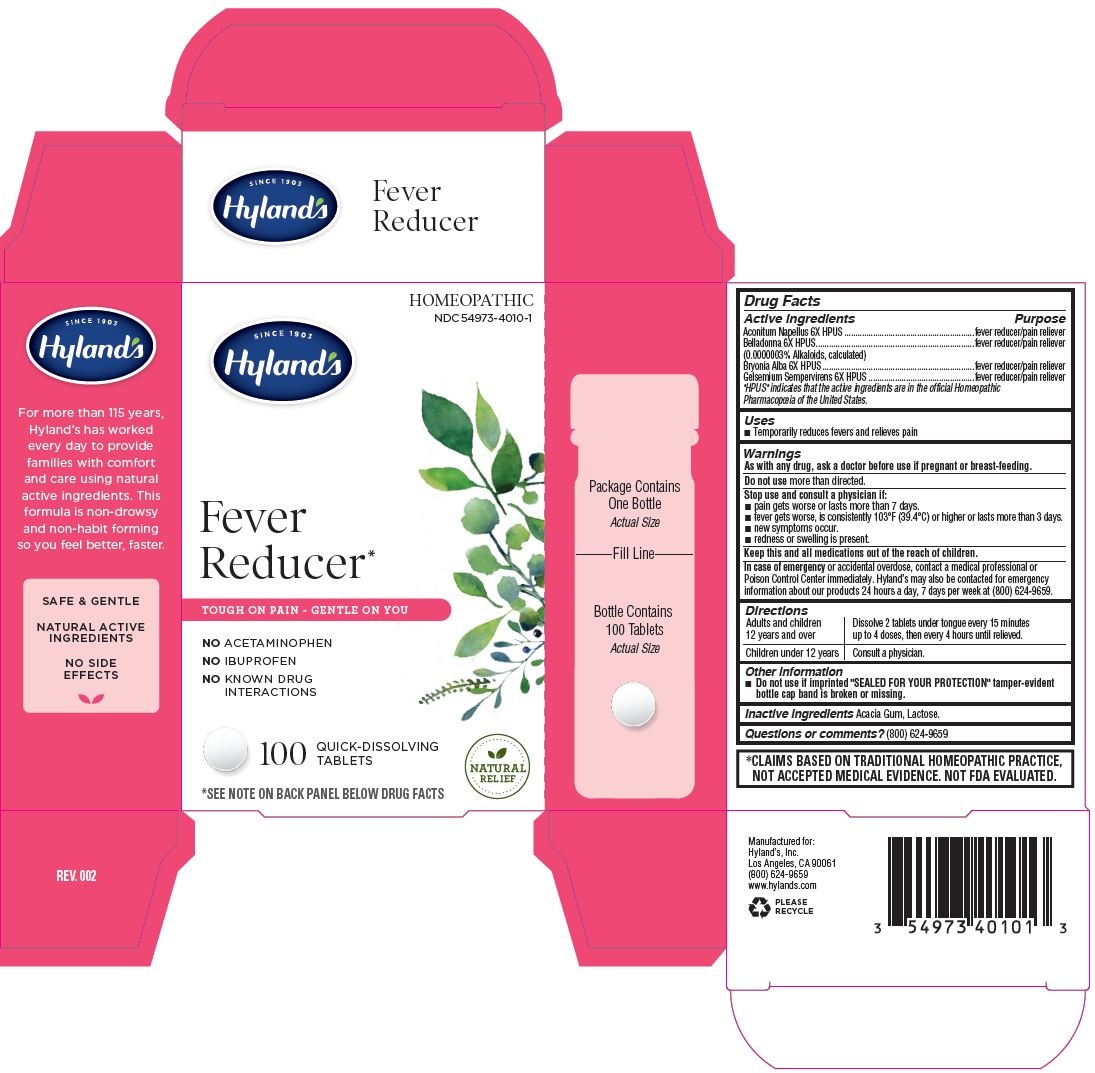 DRUG LABEL: Fever Reducer
NDC: 54973-4010 | Form: TABLET
Manufacturer: Hyland’s Inc.
Category: homeopathic | Type: HUMAN OTC DRUG LABEL
Date: 20221212

ACTIVE INGREDIENTS: ATROPA BELLADONNA 6 [hp_X]/1 1; ACONITUM NAPELLUS 6 [hp_X]/1 1; BRYONIA ALBA ROOT 6 [hp_X]/1 1; GELSEMIUM SEMPERVIRENS ROOT 6 [hp_X]/1 1
INACTIVE INGREDIENTS: LACTOSE MONOHYDRATE; ACACIA

Hyland's Fever Reducer Tablets

PURPOSE

Temporarily reduces fevers and relieves pain

Drug Facts

Active ingredients

Active ingredients | Purpose
Aconitum Napellus 6X HPUS | fever reducer/pain reliever
Belladonna 6X HPUS; (0.0000003% Alkaloids, calculated) | fever reducer/pain reliever
Bryonia Alba 6X HPUS | fever reducer/pain reliever
Gelsemium Sempervirens 6X HPUS | fever reducer/pain reliever

"HPUS" indicates that the active ingredients are in the official Homeopathic Pharmacopoeia of the United States.

Uses

■ Temporarily reduces fevers and relieves pain

Warnings

PREGNANCY OR BREAST FEEDING

As with any drug, ask a doctor before use if pregnant or breast-feeding.

Do not use more than directed.

Stop use and consult a physician if:

■ pain gets worse or lasts more than 7 days.

■ fever gets worse, is consistently 103°F (39.4°C) or higher or lasts more than 3 days.

■ new symptoms occur.

■ redness or swelling is present.

KEEP OUT OF REACH OF CHILDREN

Keep this and all medications out of the reach of children.

In case of emergency or accidental overdose, contact a medical professional or Poison Control Center immediately. Hyland’s may also be contacted for emergency information about our products 24 hours a day, 7 days per week at (800) 624-9659.

Directions

Adults and children; 12 years and over | Dissolve 2 tablets under tongue every 15 minutes; up to 4 doses, then every 4 hours until relieved.
Children under 12 years | Consult a physician.

Other information

■ Do not use if imprinted "SEALED FOR YOUR PROTECTION" tamper-evident bottle cap band is broken or missing.

Inactive ingredients

Acacia Gum, Lactose.

Questions or comments?

(800) 624-9659

*CLAIMS BASED ON TRADITIONAL HOMEOPATHIC PRACTICE,

NOT ACCEPTED MEDICAL EVIDENCE. NOT FDA EVALUATED.

Principal Display Panel

HOMEOPATHIC

NDC 54973-4010-1

SINCE 1903

Hyland's

Fever

Reducer*

TOUGH ON PAIN - GENTLE ON YOU

NO ACETAMINOPHEN

NO IBURPTOFEN

NO KNOWN DRUG

INTERACTIONS